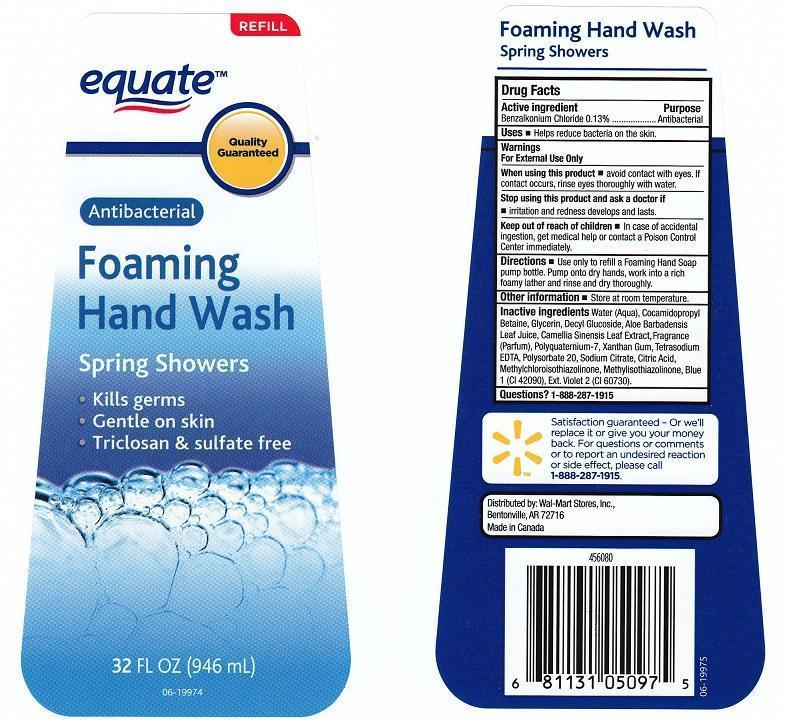 DRUG LABEL: EQUATE
NDC: 49035-014 | Form: LIQUID
Manufacturer: WAL-MART STORE INC
Category: otc | Type: HUMAN OTC DRUG LABEL
Date: 20140818

ACTIVE INGREDIENTS: BENZALKONIUM CHLORIDE 1.3 mg/1 mL
INACTIVE INGREDIENTS: WATER; COCAMIDOPROPYL BETAINE; GLYCERIN; DECYL GLUCOSIDE; ALOE VERA LEAF; GREEN TEA LEAF; POLYQUATERNIUM-7 (70/30 ACRYLAMIDE/DADMAC; 1600000 MW); XANTHAN GUM; EDETATE SODIUM; POLYSORBATE 20; SODIUM CITRATE; CITRIC ACID MONOHYDRATE; METHYLCHLOROISOTHIAZOLINONE; METHYLISOTHIAZOLINONE; FD&C BLUE NO. 1; EXT. D&C VIOLET NO. 2

DRUG FACTS

ACTIVE INGREDIENT

BENZALKONIUM CHLORIDE 0.13%

PURPOSE

ANTIBACTERIAL

USES

HELPS REDUCE BACTERIA ON THE SKIN

WARNINGS

FOR EXTERNAL USE ONLY

WHEN USING THIS PRODUCT

AVOID CONTACT WITH EYES. IF CONTACT OCCURS, RINSE EYES THOROUGHLY WITH WATER

STOP USING THIS PRODUCT AND ASK A DOCTOR IF

IRRITATION AND REDNESS DEVELOPS AND LASTS

KEEP OUT OF REACH OF CHILDREN

IN CASE OF ACCIDENTAL INGESTION, GET MEDICAL HELP OR CONTACT A POISON CONTROL CENTER IMMEDIATELY

DIRECTIONS

USE ONLY TO REFILL A FOAMING HAND SOAP PUMP BOTTLE. PUMP ONTO DRY HANDS, WORK INTO A RICH FOAMY LATHER AND RINSE AND DRY THOROUGHLY

OTHER INFORMATION

STORE AT ROOM TEMPERATURE

INACTIVE INGREDIENTS

WATER (AQUA), COCAMIDOPROPYL BETAINE, GLYCERIN, DECYL GLUCOSIDE, ALOE BARBADENSIS LEAF JUICE, CAMELLIA SINENSIS LEAF EXTRACT, FRAGRANCE (PARFUM), POLYQUATERNIUM-7, XANTHAN GUM, TETRASODIUM EDTA, POLYSORBATE 20, SODIUM CITRATE, CITRIC ACID, METHYLCHLOROISOTHIAZOLINONE, METHYLISOTHIAZOLINONE, BLUE 1 (CI 42090), EXT. VIOLET 2 (CI 60730)

QUESTIONS?

1-888-287-1915